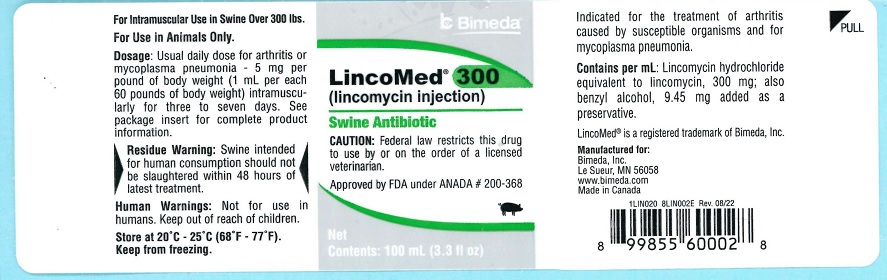 DRUG LABEL: LincoMed 300
NDC: 61133-6001 | Form: INJECTION
Manufacturer: Bimeda, Inc.
Category: animal | Type: PRESCRIPTION ANIMAL DRUG LABEL
Date: 20240327

ACTIVE INGREDIENTS: Lincomycin 300 mg/1 mL

DESCRIPTION

LincoMed® 300
(lincomycin injection)

For use in swine weighing 300 pounds or more.
For Intramuscular Use in Swine Only

CAUTION: Federal law restricts this drug to use by or on the order of a licensed veterinarian.

LincoMed 300 contains lincomycin hydrochloride, an antibiotic produced by Streptomyces lincolnensis var. lincolnensis which is chemically distinct from all other clinically available antibiotics and is isolated as a white crystalline solid.

INDICATIONS FOR SWINE:

LincoMed 300 is indicated for the treatment of infectious forms of arthritis caused by organisms sensitive to its activity. This includes most of the organisms responsible for the various infectious arthritides in swine, such as staphylococci, streptococci, Erysipelothrix and Mycoplasma spp.
It is also indicated for the treatment of mycoplasma pneumonia.

CONTRAINDICATIONS:

As with all drugs, the use of LincoMed 300 is contraindicated in animals previously found to be hypersensitive to the drug.

RESIDUE WARNING

Residue Warning: Swine intended for human consumption should not be slaughtered within 48 hours of latest treatment.

WARNINGS

Human Warnings: Not for human use. Keep out of reach of children.

PRECAUTIONS

CAUTION:

If no improvement is noted within 48 hours, consult a veterinarian.

ADVERSE REACTIONS:

The intramuscular administration to swine may cause a transient diarrhea or loose stools. Although this effect has rarely been reported, one must be alert to the possibility that it may occur.

Should this occur, it is important that the necessary steps be taken to prevent the effects of dehydration.

The Safety Data Sheet (SDS) contains more detailed occupational safety information. To report adverse drug events, for technical assistance or to obtain a copy of the SDS, contact Bimeda, Inc. at 1-888-524-6332. For additional information about adverse drug experience reporting for animal drugs, contact FDA at 1-888-FDA-VETS or online at www.fda.gov/reportanimalae.

DOSAGE AND ADMINISTRATION:

For arthritis or mycoplasma pneumonia - 5 mg/lb body weight intramuscularly once daily for three to seven days as needed. One mL per 60 lb body weight will provide 5 mg/lb.

For optimal results, initiate treatment as soon as possible.

As with any multi-dose vial, practice aseptic techniques in withdrawing each dose. Adequately clean and disinfect the vial closure prior to entry with a sterile needle and syringe. No vial closure should be entered more that 20 times.

Each mL contains:

Lincomycin hydrochloride equivalent to lincomycin 300mg; also benzyl alcohol 9.45 mg added as a preservative.

HOW SUPPLIED:

LincoMed is available in two concentrations: 100 mg/mL and 300 mg/mL.

300 mg/mL: For use in swine weighing 300 pounds or more. Supplied in 100 mL multiple dose vial.

100mg/mL: Supplied in 100 mL multiple dose vial.

STORAGE AND HANDLING

Store at 20⁰C - 25⁰C (68⁰F - 77⁰F). Keep from freezing.